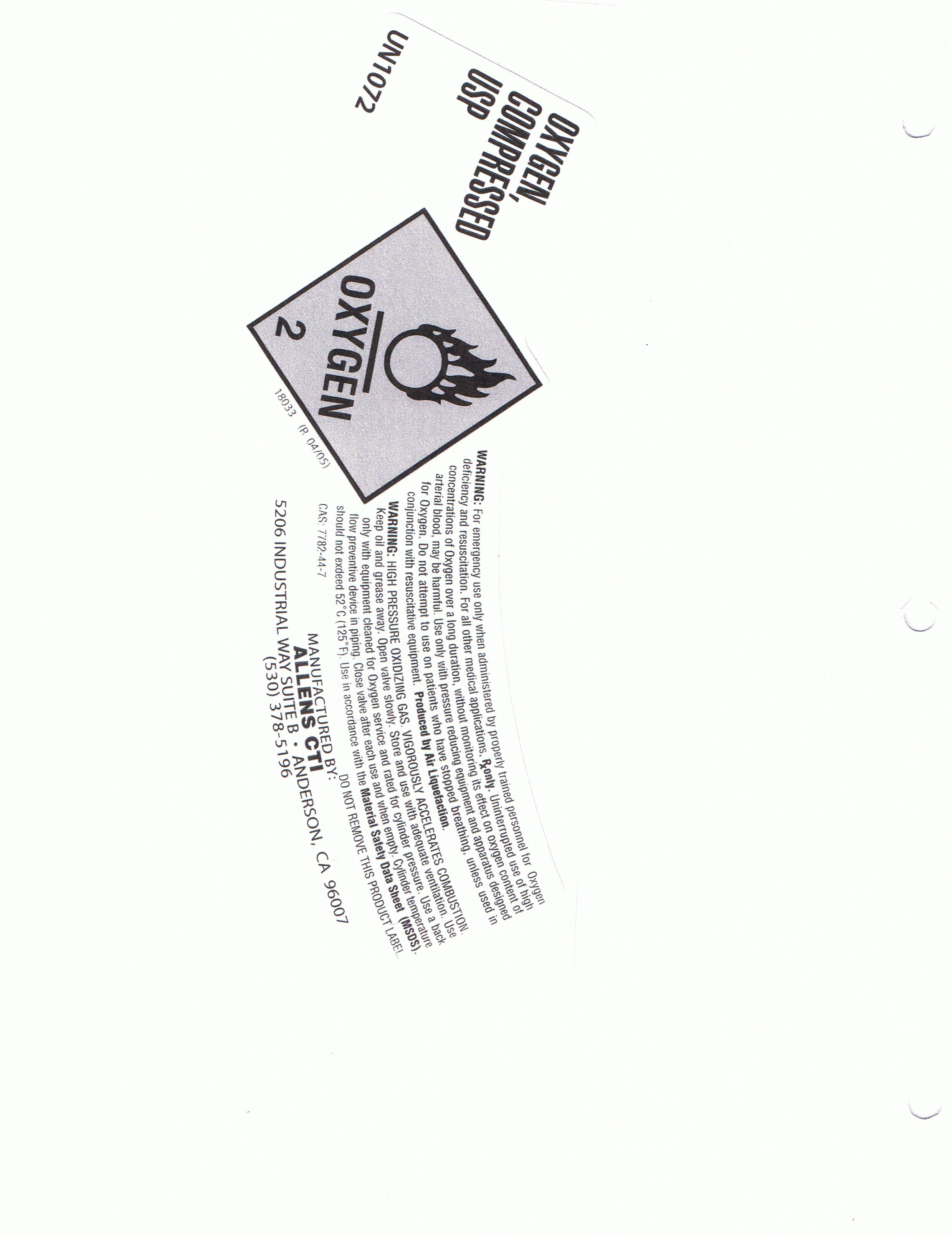 DRUG LABEL: Oxygen
NDC: 49790-001 | Form: GAS
Manufacturer: Allen's Cylinder Testing & Inspection Company
Category: prescription | Type: HUMAN PRESCRIPTION DRUG LABEL
Date: 20091104

ACTIVE INGREDIENTS: Oxygen 992 mL/1 L

PACKAGE LABEL

Oxygen, Compressed USP UN1072
WARNING: For emergency use only when administered by properly trained personnel for Oxygen deficiency and resuscitation. For all other medical applications, Rx only. Uninterrupted use of high-concentrations of Oxygen over a long duration, without monitoring its effect on oxygen content of arterial blood, may be harmful. Use only with pressure reducing equipment and apparatus designed for Oxygen. Do not attempt to use on patients who have stopped breathing, unless used in conjunction with resuscitative equipment. Produced by Air Liquefaction.
WARNING: HIGH PRESSURE OXIDIZING GAS. VIGOROUSLY ACCELERATES COMBUSTION. Keep oil and grease away. Open valve slowly. Store and use with adequate ventilation. Use only with equipment cleaned for Oxygen service and rated for cylinder pressure. Use a back flow preventive device in piping. Close valve after each use and when empty. Cylinder temperature should not exceed 52*C (125*F). Use in accordance with the Material Safety Data Sheet (MSDS).
CAS: 7782-44-7
DO NOT REMOVE THIS PRODUCT LABEL
Manufactured By:
Allens CTI
5206 Industrial Way Suite B, Anderson, CA 96007
(530) 378-5196